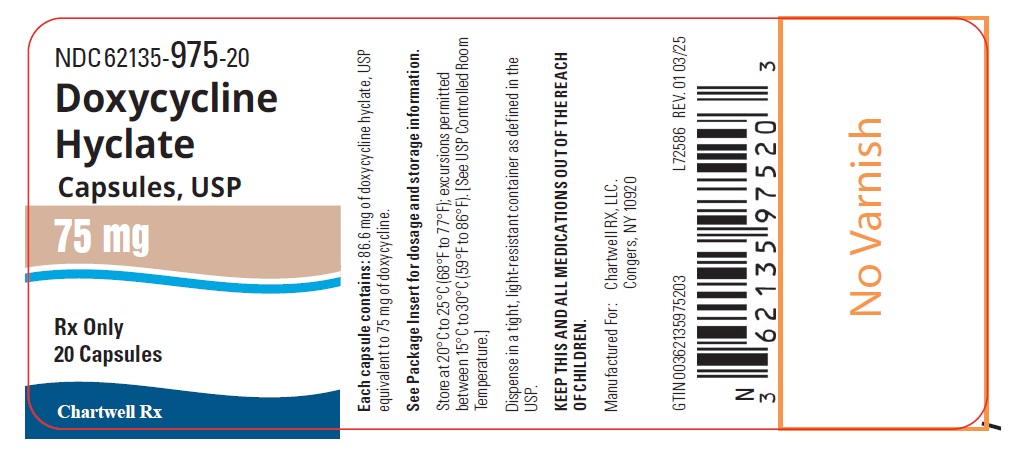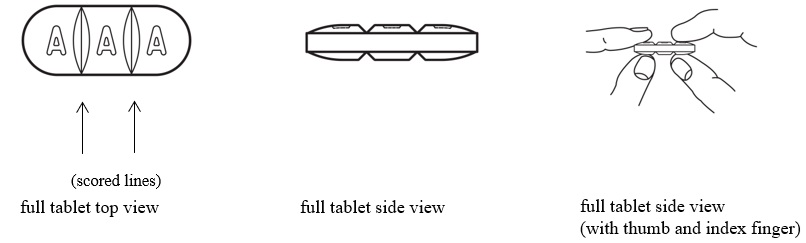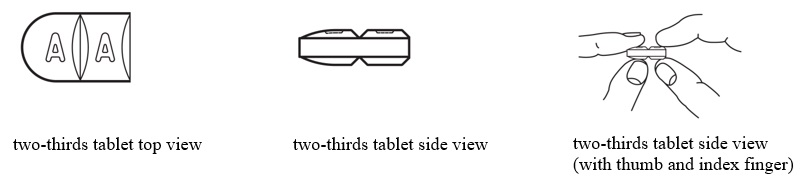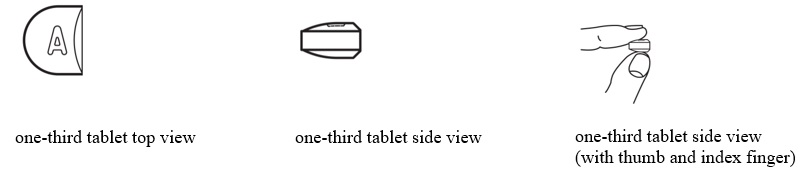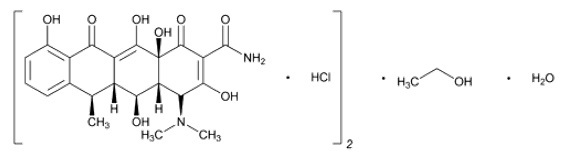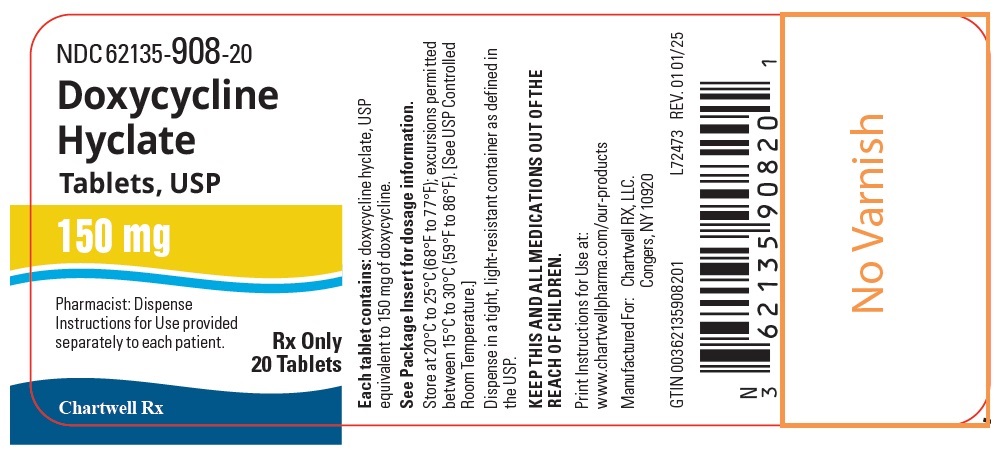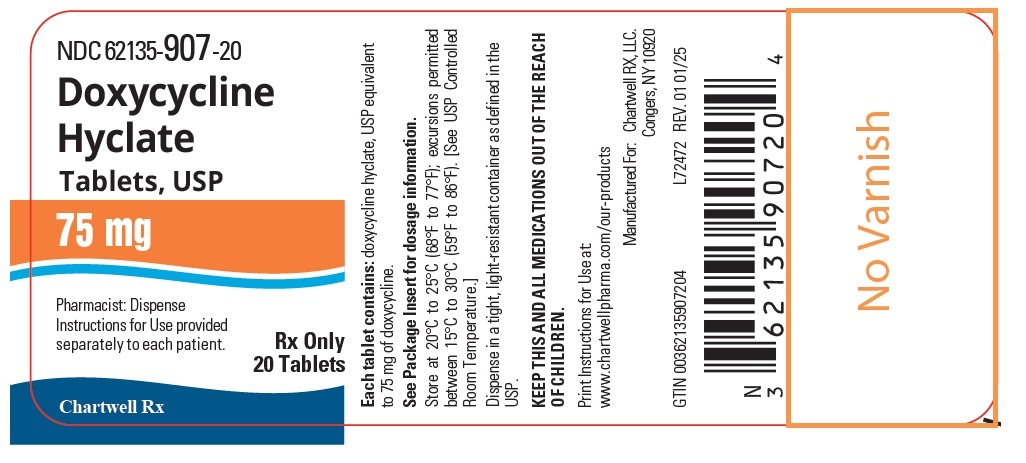 DRUG LABEL: Doxycycline Hyclate
NDC: 62135-907 | Form: TABLET, FILM COATED
Manufacturer: Chartwell RX, LLC
Category: prescription | Type: HUMAN PRESCRIPTION DRUG LABEL
Date: 20250411

ACTIVE INGREDIENTS: DOXYCYCLINE HYCLATE 75 mg/1 1
INACTIVE INGREDIENTS: CROSCARMELLOSE SODIUM; MAGNESIUM STEARATE; MICROCRYSTALLINE CELLULOSE; SODIUM LAURYL SULFATE; FD&C BLUE NO. 2; POLYVINYL ALCOHOL, UNSPECIFIED; POLYETHYLENE GLYCOL 8000; TALC; TITANIUM DIOXIDE

HIGHLIGHTS OF PRESCRIBING INFORMATION

Doxycycline Hyclate Tablets and Doxycycline Hyclate Capsules
These highlights do not include all the information needed to use DOXYCYCLINE HYCLATE TABLETS and DOXYCYCLINE HYCLATE CAPSULES safely and effectively. See full prescribing information for DOXYCYCLINE HYCLATE TABLETS and DOXYCYCLINE HYCLATE CAPSULES.
DOXYCYCLINE HYCLATE tablets, for oral use
DOXYCYCLINE HYCLATE capsules, for oral use
Initial U.S. Approval: 1967

RECENT MAJOR CHANGES

Warnings and Precautions, Severe Skin Reactions (5.5) 04/2025

1 INDICATIONS AND USAGE

Doxycycline hyclate tablets and doxycycline hyclate capsules are tetracycline class drugs indicated for:

- Rickettsial infections (1.1)
- Sexually transmitted infections (1.2)
- Respiratory tract infections (1.3)
- Specific bacterial infections (1.4)
- Ophthalmic infections (1.5)
- Anthrax, including inhalational anthrax (post-exposure) (1.6)
- Alternative treatment for selected infections when penicillin is contraindicated (1.7)
- Adjunctive therapy for acute intestinal amebiasis and severe acne (1.8)
- Prophylaxis of malaria (1.9)

To reduce the development of drug-resistant bacteria and maintain the effectiveness of doxycycline hyclate and other antibacterial drugs, doxycycline hyclate should be used only to treat or prevent infections that are proven or strongly suspected to be caused by bacteria. (1.10)

2 DOSAGE AND ADMINISTRATION

- Important Administration Instructions for doxycycline hyclate tablets and doxycycline hyclate capsules:
  - Doxycycline hyclate tablets (150 mg) can be broken into two-thirds or one-third to provide a 50 mg and 100 mg strength, respectively. (2.1)
  - Swallow doxycycline hyclate capsule whole. Do not break, open, crush, dissolve or chew the capsule. (2.1)
- Dosage in Adults for doxycycline hyclate tablets and doxycycline hyclate capsules:
  - The usual dosage is 200 mg on the first day of treatment (administered 100 mg every 12 hours) followed by a maintenance dose of 100 mg daily. (2.1)
  - In the management of more severe infections (particularly chronic infections of the urinary tract), 100 mg every 12 hours is recommended. (2.1)
- Dosage in Pediatric Patients for doxycycline hyclate tablets and doxycycline hyclate capsules:
  - For all pediatric patients weighing less than 45 kg with severe or life-threatening infections (e.g., anthrax, Rocky Mountain spotted fever), the recommended dose is 2.2 mg per kg of body weight administered every 12 hours. Pediatric patients weighing 45 kg or more should receive the adult dose. (2.3)
  - For pediatric patients with less severe disease (greater than 8 years of age and weighing less than 45 kg), the recommended dose is 4.4 mg per kg of body weight divided into two doses on the first day of treatment, followed by a maintenance dose of 2.2 mg per kg of body weight (given as a single daily dose or divided into two doses. For pediatric patients weighing over 45 kg, the usual adult dose should be used. (2.3)

- See Full Prescribing Information for additional indication specific dosage information and important administration instructions for doxycycline hyclate tablets and doxycycline hyclate capsules. (2.1, 2.4, 2.5)

3 DOSAGE FORMS AND STRENGTHS

- Doxycycline Hyclate Tablets, USP: 75 mg and 150 mg (functionally scored) (3)
- Doxycycline Hyclate Capsules, USP: 75 mg (3)

4 CONTRAINDICATIONS

Doxycycline hyclate are contraindicated in persons who have shown hypersensitivity to any of the tetracyclines. (4)

5 WARNINGS AND PRECAUTIONS

- The use of doxycycline hyclate during tooth development (last half of pregnancy, infancy and childhood to the age of 8 years) may cause permanent discoloration of the teeth (yellow-gray-brown) and enamel hypoplasia Advise the patient of the potential risk to the fetus during pregnancy. (2.2, 5.1, 8.1, 8.4)
- The use of doxycycline hyclate during the second and third-trimester of pregnancy, infancy and childhood up to the age of 8 years may cause reversible inhibition of bone growth. Advise the patient of the potential risk to the fetus during pregnancy. (5.2, 8.1, 8.4)
- Clostridioidesdifficile-associated diarrhea (CDAD) has been reported. Evaluate patients if diarrhea occurs. (5.3)
- Photosensitivity manifested by an exaggerated sunburn reaction has been observed in some individuals taking tetracyclines. Limit sun exposure. (5.4)
- Overgrowth of non-susceptible organisms, including fungi, may occur. If such infections occur, discontinue use and institute appropriate therapy. (5.10)

6 ADVERSE REACTIONS

Adverse reactions observed in patients receiving tetracyclines include anorexia, nausea, vomiting, diarrhea, rash, photosensitivity, urticaria, and hemolytic anemia. (6)

To report SUSPECTED ADVERSE REACTIONS, contact Chartwell RX, LLC. at 1-845-232-1683, or FDA at 1-800-FDA-1088 or www.fda.gov/medwatch.

7 DRUG INTERACTIONS

- Patients who are on anticoagulant therapy may require downward adjustment of their anticoagulant dosage. (7.1)
- Avoid co-administration of tetracyclines with penicillin. (7.2)
- Absorption of tetracyclines, including doxycycline hyclate is impaired by antacids containing aluminum, calcium, or magnesium, bismuth subsalicylate and iron-containing preparations. (7.3)
- Concurrent use of tetracyclines, including doxycycline hyclate may render oral contraceptives less effective. (7.4)
- Barbiturates, carbamazepine and phenytoin decrease the half-life of doxycycline. (7.5)

8 USE IN SPECIFIC POPULATIONS

- Lactation: Breastfeeding is not recommended. (8.2)

FULL PRESCRIBING INFORMATION

1 INDICATIONS AND USAGE

1.1 Rickettsial Infections

Doxycycline hyclate tablets and capsules are indicated for treatment of Rocky Mountain spotted fever, typhus fever and the typhus group, Q fever, rickettsial pox, and tick fevers caused by Rickettsiae.

1.2 Sexually Transmitted Infections

Doxycycline hyclate tablets and capsules are indicated for treatment of the following sexually transmitted infections:

- Uncomplicated urethral, endocervical or rectal infections caused by Chlamydia trachomatis.
- Nongonococcal urethritis caused by Ureaplasma urealyticum.
- Lymphogranuloma venereum caused by Chlamydia trachomatis.
- Granuloma inguinale caused by Klebsiella granulomatis.
- Uncomplicated gonorrhea caused by Neisseria gonorrhoeae.
- Chancroid caused by Haemophilus ducreyi.

1.3 Respiratory Tract Infections

Doxycycline hyclate tablets and capsules are indicated for treatment of the following respiratory tract infections:

- Respiratory tract infections caused by Mycoplasma pneumoniae.
- Psittacosis (ornithosis) caused by Chlamydophila psittaci.
- Because many strains of the following groups of microorganisms have been shown to be resistant to doxycycline, culture and susceptibility testing are recommended.
- Doxycycline is indicated for treatment of infections caused by the following microorganisms, when bacteriological testing indicates appropriate susceptibility to the drug:
- Respiratory tract infections caused by Haemophilus influenzae.
- Respiratory tract infections caused by Klebsiella species.
- Upper respiratory infections caused by Streptococcus pneumoniae.

1.4 Specific Bacterial Infections

Doxycycline hyclate tablets and capsules are indicated for treatment of the following specific bacterial infections:

- Relapsing fever due to Borrelia recurrentis.
- Plague due to Yersinia pestis.
- Tularemia due to Francisella tularensis.
- Cholera caused by Vibrio cholerae.
- Campylobacter fetus infections caused by Campylobacter fetus.
- Brucellosis due to Brucellaspecies (in conjunction with streptomycin).
- Bartonellosis due to Bartonella bacilliformis.

Because many strains of the following groups of microorganisms have been shown to be resistant to doxycycline, culture and susceptibility testing are recommended.

Doxycycline hyclate tablets and capsules are indicated for treatment of infections caused by the following gram-negative microorganisms, when bacteriological testing indicates appropriate susceptibility to the drug:

- Escherichia coli
- Enterobacter aerogenes
- Shigellaspecies
- Acinetobacterspecies
- Urinary tract infections caused by Klebsiellaspecies.

1.5 Ophthalmic Infections

Doxycycline hyclate tablets and capsules are indicated for treatment of the following ophthalmic infections:

- Trachoma caused by Chlamydia trachomatis, although the infectious agent is not always eliminated as judged by immunofluorescence.
- Inclusion conjunctivitis caused by Chlamydia trachomatis.

1.6 Anthrax Including Inhalational Anthrax (Post-Exposure)

Doxycycline hyclate tablets and capsules are indicated for the treatment of Anthrax due to Bacillus anthracis, including inhalational anthrax (post-exposure); to reduce the incidence or progression of disease following exposure to aerosolized Bacillus anthracis.

1.7 Alternative Treatment for Selected Infections when Penicillin is Contraindicated

Doxycycline hyclate tablets and capsules are indicted as an alternative treatment for the following selected infections when penicillin is contraindicated:

- Syphilis caused by Treponema pallidum.
- Yaws caused by Treponema pallidumsubspecies pertenue.
- Listeriosis due to Listeria monocytogenes.
- Vincent’s infection caused by Fusobacterium fusiforme.
- Actinomycosis caused by Actinomyces israelii.
- Infections caused by Clostridiumspecies.

1.8 Adjunctive Therapy for Acute Intestinal Amebiasis and Severe Acne

In acute intestinal amebiasis, doxycycline hyclate tablets and capsules may be a useful adjunct to amebicides.

In severe acne, doxycycline hyclate tablets and capsules may be useful adjunctive therapy.

1.9 Prophylaxis of Malaria

Doxycycline hyclate tablets and capsules are indicated for the prophylaxis of malaria due to Plasmodium falciparumin short-term travelers (less than 4 months) to areas with chloroquine and/or pyrimethamine-sulfadoxine resistant strains [see Dosage and Administration (2.4)and Patient Counseling Information (17)].

1.10 Usage

To reduce the development of drug-resistant bacteria and maintain the effectiveness of doxycycline hyclate and other antibacterial drugs, doxycycline hyclate should be used only to treat or prevent infections that are proven or strongly suspected to be caused by susceptible bacteria. When culture and susceptibility information are available, they should be considered in selecting or modifying antibacterial therapy. In the absence of such data, local epidemiology and susceptibility patterns may contribute to the empiric selection of therapy.

2 DOSAGE AND ADMINISTRATION

2.1 Important Administration Instructions

- The usual dosage and frequency of administration of doxycycline hyclate tablets and capsules differs from that of the other tetracyclines. Exceeding the recommended dosage may result in an increased incidence of adverse reactions.
- Administer doxycycline hyclate tablets and capsules with adequate amounts of fluid to wash down the drugs and reduce the risk of esophageal irritation and ulceration [see Adverse Reactions (6)] .
- If gastric irritation occurs, doxycycline hyclate tablets and capsules may be given with food or milk [see Clinical Pharmacology (12.3)]
- Swallow doxycycline hyclate capsules whole. Do not break, open, crush, dissolve or chew the capsule.
- Doxycycline hyclate tablets (150 mg) can be broken into two-thirds or one-third to provide a 100 mg and 50 mg strength, respectively [see FDA-approved patient labeling].

2.2 Dosage in Adult Patients

- The usual dosage of doxycycline hyclate tablet is 200 mg on the first day of treatment (administered 100 mg every 12 hours) followed by a maintenance dose of 100 mg daily. The maintenance dose may be administered as a single dose or as 50 mg every 12 hours.
- In the management of more severe infections (particularly chronic infections of the urinary tract), 100 mg every 12 hours is recommended.
- For certain selected specific indications, the recommended duration or dosage and duration of doxycycline hyclate tablets and capsules in adult patients are as follows:

1. Streptococcal infections, therapy should be continued for 10 days.
2. Uncomplicated urethral, endocervical, or rectal infection caused by Chlamydia trachomatis: 100 mg by mouth twice-a-day for 7 days.
3. Uncomplicated gonococcal infections in adults (except anorectal infections in men): 100 mg, by mouth, twice-a-day for 7 days. As an alternate single visit dose, administer 300 mg stat followed in one hour by a second 300 mg dose.
4. Nongonococcal urethritis (NGU) caused by C. trachomatisand U. urealyticum:100 mg by mouth twice‑a‑day for 7 days.
5. Syphilis – early: Patients who are allergic to penicillin should be treated with doxycycline 100 mg by mouth twice-a-day for 2 weeks.
6. Syphilis of more than one year’s duration: Patients who are allergic to penicillin should be treated with doxycycline 100 mg by mouth twice-a-day for 4 weeks.
7. Acute epididymo-orchitis caused by N. gonorrhoeae: 100 mg by mouth, twice-a-day for at least 10 days.
8. Acute epididymo-orchitis caused by C. trachomatis: 100 mg, by mouth, twice-a-day for at least 10 days.

2.3 Dosage in Pediatric Patients

- For all pediatric patients weighing less than 45 kg with severe or life threatening infections (e.g., anthrax, Rocky Mountain spotted fever), the recommended dosage of doxycycline hyclate tablet and capsule is 2.2 mg per kg of body weight administered every 12 hours. Pediatric patients weighing 45 kg or more should receive the adult dose [see Warnings and Precautions (5.1)].
- For pediatric patients with less severe disease (greater than 8 years of age and weighing less than 45 kg), the recommended dosage schedule of doxycycline hyclate tablet and capsule is 4.4 mg per kg of body weight divided into two doses on the first day of treatment, followed by a maintenance dose of 2.2 mg per kg of body weight (given as a single daily dose or divided into twice daily doses). For pediatric patients weighing over 45 kg, the usual adult dose should be used.

2.4 Dosage for Prophylaxis of Malaria

For adults, the recommended dose of doxycycline hyclate tablet is 100 mg daily.

For pediatric patients 8 years of age and older, the recommended dosage of doxycycline hyclate tablet and capsule is 2 mg per kg of body weight administered once daily. Pediatric patients weighing 45 kg or more should receive the adult dose.

Prophylaxis should begin 1 or 2 days before travel to the malarious area. Prophylaxis should be continued daily during travel in the malarious area and for 4 weeks after the traveler leaves the malarious area.

2.5 Dosage for Inhalational Anthrax (Post-Exposure)

For adults, the recommended dosage is 100 mg, of doxycycline hyclate tablet and capsule, by mouth, twice-a-day for 60 days.

For pediatric patients weighing less than 45 kg, the recommended dosage of doxycycline hyclate tablet is 2.2 mg per kg of body weight, by mouth, twice-a-day for 60 days. Pediatric patients weighing 45 kg or more should receive the adult dose.

3 DOSAGE FORMS AND STRENGTHS

Doxycycline Hyclate Tablets, USP:

Doxycycline Hyclate Tablets, USP 75 mg are round convex light blue, film-coated, compressed tablet with “ 75'' debossed on one side of the tablet and "AQ"over "101"debossed on the other (each tablet contains 75 mg doxycycline as 86.6 mg doxycycline hyclate).

Doxycycline Hyclate Tablets, USP 150 mg are capsule-shaped, convex, mossy-green, film-coated compressed tablet. Each side of the tablet is trisected with an " A" debossed on each portion of one side of the tablet, and no debossing on the other (each tablet contains 150 mg doxycycline as 173.1 mg doxycycline hyclate).

Doxycycline Hyclate Capsules, USP:

Doxycycline Hyclate Capsules, USP 75 mg are size #2, hard gelatin capsules, blue opaque cap with white opaque body, imprinted with “ CE” on the cap and “ 227” on the body in black ink, filled with yellow powder (each capsule contains 75 mg doxycycline as 86.6 mg doxycycline hyclate).

4 CONTRAINDICATIONS

Doxycycline hyclate are contraindicated in persons who have shown hypersensitivity to any of the tetracyclines.

5 WARNINGS AND PRECAUTIONS

5.1 Tooth Development

The use of doxycycline hyclate during tooth development (last half of pregnancy, infancy and childhood to the age of 8 years) may cause permanent discoloration of the teeth (yellow-gray-brown). This adverse reaction is more common during long-term use of the drugs of the tetracycline class, but it has been observed following repeated short-term courses. Enamel hypoplasia has also been reported with drugs of the tetracycline class. Advise the patient of the potential risk to the fetus if doxycycline hyclate is used during pregnancy [see Use in Specific Populations (8.1, 8.4)].

Use doxycycline hyclate in pediatric patients 8 years of age or less only when the potential benefits are expected to outweigh the risks in severe or life-threatening conditions (e.g., anthrax, Rocky Mountain spotted fever), particularly when there are no alternative therapies.

5.2 Inhibition of Bone Growth

The use of doxycycline hyclate during the second and third trimester of pregnancy, infancy and childhood up to the age of 8 years may cause reversible inhibition of bone growth. All tetracyclines form a stable calcium complex in any bone-forming tissue. A decrease in fibula growth rate has been observed in premature infants given oral tetracycline in doses of 25 mg/kg every 6 hours. This reaction was shown to be reversible when the drug was discontinued. Advise the patient of the potential risk to the fetus if doxycycline hyclate tablets and capsules are used during pregnancy [see Use in Specific Populations (8.1, 8.4)] .

5.3 Clostridioides difficileAssociated Diarrhea

Clostridioides difficileassociated diarrhea (CDAD) has been reported with use of nearly all antibacterial agents, including doxycycline hyclate , and may range in severity from mild diarrhea to fatal colitis. Treatment with antibacterial agents alters the normal flora of the colon leading to overgrowth of C. difficile.

C. difficileproduces toxins A and B which contribute to the development of CDAD. Hypertoxin producing strains of C. difficilecause increased morbidity and mortality, as these infections can be refractory to antibacterial therapy and may require colectomy. CDAD must be considered in all patients who present with diarrhea following antibacterial use. Careful medical history is necessary since CDAD has been reported to occur over two months after the administration of antibacterial agents.

If CDAD is suspected or confirmed, ongoing antibacterial use not directed against C. difficilemay need to be discontinued. Appropriate fluid and electrolyte management, protein supplementation, antibacterial treatment of C. difficile,and surgical evaluation should be instituted as clinically indicated.

5.4 Photosensitivity

Photosensitivity manifested by an exaggerated sunburn reaction has been observed in some individuals taking tetracyclines. Patients apt to be exposed to direct sunlight or ultraviolet light should be advised that this reaction can occur with tetracycline drugs, and treatment should be discontinued at the first evidence of skin erythema.

5.5 Severe Skin Reactions

Severe skin reactions, such as exfoliative dermatitis, erythema multiforme, Stevens-Johnson syndrome, toxic epidermal necrolysis, and drug reaction with eosinophilia and systemic symptoms (DRESS) have been reported in patients receiving doxycycline. Fixed drug eruptions have occurred with doxycycline and have been associated with worsening severity upon subsequent administrations, including generalized bullous fixed drug eruption [See Adverse Reactions (6)] . If severe skin reactions occur, discontinue doxycycline hyclate tablets and doxycycline hyclate capsules immediately and institute appropriate therapy.

5.6 Intracranial Hypertension

Intracranial hypertension (IH, pseudotumor cerebri) has been associated with the use of tetracyclines including doxycycline hyclate. Clinical manifestations of IH include headache, blurred vision, diplopia, and vision loss; papilledema can be found on fundoscopy. Women of childbearing age who are overweight or have a history of IH are at greater risk for developing tetracycline associated IH. Concomitant use of isotretinoin and doxycycline hyclate should be avoided because isotretinoin is also known to cause pseudotumor cerebri.

Although IH typically resolves after discontinuation of treatment, the possibility for permanent visual loss exists. If visual disturbance occurs during treatment, prompt ophthalmologic evaluation is warranted. Since intracranial pressure can remain elevated for weeks after drug cessation patients should be monitored until they stabilize.

5.7 Antianabolic Action

The antianabolic action of the tetracyclines may cause an increase in BUN. Studies to date indicate that this does not occur with the use of doxycycline in patients with impaired renal function.

5.8 Incomplete Suppression of Malaria

Doxycycline offers substantial but not complete suppression of the asexual blood stages of Plasmodiumstrains.

Doxycycline does not suppress P. falciparum’ssexual blood stage gametocytes. Subjects completing this prophylactic regimen may still transmit the infection to mosquitoes outside endemic areas.

5.9 Development of Drug-Resistant Bacteria

Prescribing doxycycline hyclate in the absence of a proven or strongly suspected bacterial infection or a prophylactic indication is unlikely to provide benefit to the patient and increases the risk of the development of drug-resistant bacteria.

5.10 Potential for Microbial Overgrowth

Doxycycline hyclate may result in overgrowth of non-susceptible organisms, including fungi. If such infections occur, discontinue use and institute appropriate therapy.

5.11 Laboratory Monitoring for Long-Term Therapy

In long-term therapy, periodic laboratory evaluation of organ systems, including hematopoietic, renal and hepatic studies should be performed.

6 ADVERSE REACTIONS

The following adverse reactions have been identified during clinical trials or post-approval use of tetracycline-class drugs, including doxycycline. Because these reactions are reported voluntarily from a population of uncertain size, it is not always possible to reliably estimate their frequency or establish a causal relationship to drug exposure.

Gastrointestinal:Anorexia, nausea, vomiting, diarrhea, glossitis, dysphagia, enterocolitis, inflammatory lesions (with monilial overgrowth) in the anogenital region, and pancreatitis. Hepatotoxicity has been reported. These reactions have been caused by both the oral and parenteral administration of tetracyclines. Superficial discoloration of the adult permanent dentition, reversible upon drug discontinuation and professional dental cleaning has been reported. Permanent tooth discoloration and enamel hypoplasia may occur with drugs of the tetracycline class when used during tooth development [See Warnings and Precautions (5.1)] . Instances of esophagitis and esophageal ulcerations have been reported in patients receiving capsule and tablet forms of drugs in the tetracycline-class. Most of these patients took medications immediately before going to bed [see Dosage and Administration (2.1)] .

Skin:Maculopapular and erythematous rashes, Stevens-Johnson syndrome, toxic epidermal necrolysis, exfoliative dermatitis, erythema multiforme, and fixed drug eruption have been reported. Photosensitivity has been reported [see Warnings and Precautions (5.4)] .

Renal:Rise in BUN has been reported and is apparently dose-related [see Warnings and Precautions (5.7)] .

Hypersensitivity reactions:Urticaria, angioneurotic edema, anaphylaxis, anaphylactoid purpura, serum sickness, pericarditis, exacerbation of systemic lupus erythematosus, and drug reaction with eosinophilia and systemic symptoms (DRESS).

Blood:Hemolytic anemia, thrombocytopenia, neutropenia, and eosinophilia have been reported.

Intracranial Hypertension:Intracranial hypertension (IH, pseudotumor cerebri) has been associated with the use of tetracyclines [see Warnings and Precautions (5.6)] .

Thyroid Gland Changes:When given over prolonged periods, tetracyclines have been reported to produce brown-black microscopic discoloration of thyroid glands. No abnormalities of thyroid function are known to occur.

Psychiatric:Depression, anxiety, suicidal ideation, insomnia, abnormal dreams, hallucination.

7 DRUG INTERACTIONS

7.1 Anticoagulant Drugs

Because tetracyclines have been shown to depress plasma prothrombin activity, patients who are on anticoagulant therapy may require downward adjustment of their anticoagulant dosage.

7.2 Penicillin

Since bacteriostatic drugs may interfere with the bactericidal action of penicillin, it is advisable to avoid giving tetracyclines, including doxycycline hyclate in conjunction with penicillin.

7.3 Antacids and Iron Preparations

Absorption of tetracyclines, including doxycycline hyclate is impaired by antacids containing aluminum, calcium, or magnesium, bismuth subsalicylate, and iron-containing preparations.

7.4 Oral Contraceptives

Concurrent use of tetracyclines, including doxycycline hyclate may render oral contraceptives less effective.

7.5 Barbiturates and Anti-Epileptics

Barbiturates, carbamazepine, and phenytoin decrease the half-life of doxycycline.

7.7 Drug and Laboratory Test Interactions

False elevations of urinary catecholamines may occur due to interference with the fluorescence test.

8 USE IN SPECIFIC POPULATIONS

8.1 Pregnancy

Risk Summary

Doxycycline hyclate, like other tetracycline-class antibacterial drugs, may cause discoloration deciduous teeth, and reversible inhibition of bone growth when administered during the second and third trimester of pregnancy [see Warnings and Precautions (5.1) and (5.2)]. Available data from published studies over decades have not shown a difference in major birth defect risk compared to unexposed pregnancies with doxycycline exposure in the first trimester of pregnancy (see Data). There are no available data on the risk of miscarriage following exposure to doxycycline in pregnancy. Advise the patient of the potential risk to the fetus if doxycycline hyclate is used during pregnancy.

The estimated background risk of major birth defects and miscarriage for the indicated population is unknown. All pregnancies have a background risk of birth defect, loss, or other adverse outcomes. In the U.S. general population, the estimated background risk of major birth defects and miscarriage in clinically recognized pregnancies is 2% to 4% and 15% to 20%, respectively.

Data

Human Data

A retrospective cohort study of 1,690 pregnant patients who received doxycycline prescriptions in the first trimester of pregnancy compared to an unexposed pregnant cohort showed no difference in the major malformation rate. There is no information on the dose or duration of treatment, or if the patients actually ingested the doxycycline that was prescribed.

Other published studies on exposure to doxycycline in the first trimester of pregnancy have small sample sizes; however, these studies have not shown an increased risk of major malformations.

The use of tetracyclines during tooth development (second and third trimester of pregnancy) may cause permanent discoloration of the teeth (yellow-gray-brown). This adverse reaction is more common during long-term use of the drug but has been observed following repeated short-term courses. [see Warnings and Precautions (5.1, 5.2)].

Animal Data

Results of animal studies indicate that tetracyclines cross the placenta, are found in fetal tissues, and can have toxic effects on the developing fetus (often related to retardation of skeletal development). Evidence of embryotoxicity also has been noted in animals treated early in pregnancy.

8.2 Lactation

Risk Summary

Based on available published data, doxycycline is present in human milk. There are no data that inform the levels of doxycycline in breastmilk, the effects on the breastfed infant, or the effects on milk production. Because of the potential for serious adverse reactions, including tooth discoloration and inhibition of bone growth, advise patients that breastfeeding is not recommended during treatment with doxycycline hyclate and for 5 days after the last dose.

8.3 Females and Males of Reproductive Potential

Infertility

Based on findings from a fertility study in animals, doxycycline may impair female and male fertility. The reversibility of this finding is unclear. [see Nonclinical Toxicology (13.1)] .

8.4 Pediatric Use

Because of the effects of drugs of the tetracycline-class on tooth development and growth, use doxycycline hyclate in pediatric patients 8 years of age or less only when the potential benefits are expected to outweigh the risks in severe or life-threatening conditions (e.g., anthrax, Rocky Mountain spotted fever), particularly when there are no alternative therapies [see Warnings and Precautions (5.1, 1.1) and Dosage and Administration (2.1, 2.5)] .

8.5 Geriatric Use

Clinical studies of doxycycline hyclate tablets did not include sufficient numbers of subjects aged 65 and over to determine whether they respond differently from younger subjects. Other reported clinical experience has not identified differences in responses between the elderly and younger patients. Doxycycline hyclate tablets each contains less than 1 mg of sodium.

10 OVERDOSAGE

In case of overdosage, discontinue medication, treat symptomatically and institute supportive measures. Dialysis does not alter serum half-life and thus would not be of benefit in treating cases of overdosage.

11 DESCRIPTION

Doxycycline Hyclate Tablets, USP and and Doxycycline Hyclate Capsules, USP contain Doxycycline Hyclate, USP a tetracycline class drug synthetically derived from oxytetracycline, in an immediate release formulation for oral administration.

The molecular formula of doxycycline hyclate is (C22H24N2O8•HCl)2•C2H6O•H2O and the molecular weight of doxycycline hyclate is 1025.87. The chemical name for doxycycline hyclate is:

4-(Dimethylamino)-1,4,4a,5,5a,6,11,12a-octahydro-3,5,10,12,12a-pentahydroxy-6-methyl-1,11-dioxo-2-naphthacenecarboxamide monohydrochloride, compound with ethyl alcohol (2:1), monohydrate.

The structural formula for doxycycline hyclate is:

Figure 1: Structure of Doxycycline Hyclate

Doxycycline hyclate is a yellow crystalline powder soluble in water and in solutions of alkali hydroxides and carbonates.

Doxycycline Hyclate Tablets, USP :

Doxycycline Hyclate Tablets, USP are available as 75 mg and 150 mg tablets. Each 75 mg tablet contains 86.6 mg of doxycycline hyclate equivalent to 75 mg of doxycycline. Each 150 mg tablet contains 173.1 mg of doxycycline hyclate equivalent to 150 mg of doxycycline.

Inactive ingredients in the tablet formulation are croscarmellose sodium, magnesium stearate, microcrystalline cellulose and sodium lauryl sulfate. Film-coating contains: FD&C Blue#2/Indigotine Aluminum Lake, polyvinyl alcohol, polyethylene glycol 8000, talc, titanium dioxide and yellow iron oxide (150 mg Tablet). Doxycycline Hyclate Tablets, USP 75 mg contain 0.95 mg (0.041 mEq) of sodium. Doxycycline Hyclate Tablets, USP 150 mg contain 1.89 mg (0.082 mEq) of sodium.

Doxycycline Hyclate Capsules, USP:

Doxycycline Hyclate Capsules, USP are available as 75 mg capsules. Each 75 mg capsule contains 86.6 mg of doxycycline hyclate equivalent to 75 mg of doxycycline.

Inactive ingredients in the capsule formulation are magnesium stearate, microcrystalline cellulose, and a hard gelatin capsule which contains FD&C Blue #1, FD&C Red #3 and titanium dioxide. The capsules are printed with edible ink containing alcohol, black iron oxide, FD&C Blue #1/ Brilliant Blue FCF Aluminum Lake, FD&C Blue #2/Indigo Carmine Aluminum Lake, FD&C Red #40/Allura Red AC Aluminum Lake, D&C Yellow #10 Aluminum Lake, and shellac glaze.

12 CLINICAL PHARMACOLOGY

12.1 Mechanism of Action

Doxycycline is a tetracycline-class antimicrobial drug [see Microbiology (12.4)] .

12.3 Pharmacokinetics

Absorption

Doxycycline hyclate tablets: Following administration of a single 300 mg dose to adult volunteers, average peak plasma doxycycline levels were 3.0 mcg per mL at 3 hours, decreasing to 1.18 mcg per mL at 24 hours. The mean Cmaxand AUC0-∞of doxycycline are 24% and 15% lower, respectively, following single dose administration of doxycycline hyclate tablets, 150 mg tablets with a high fat meal (including milk) compared to fasted conditions. The clinical significance of these decreases is unknown.

Doxycycline hyclate capsules : Following administration of a single 300 mg dose to adult volunteers, average peak plasma doxycycline levels were 2.8 mcg per mL at 3 hours, decreasing to 1.1 mcg per mL at 24 hours. The mean Cmaxof doxycycline is approximately 20% lower and the AUC0-∞is unchanged following single dose administration of doxycycline hyclate capsules with a high fat meal (including milk) compared to fasted conditions. The clinical significance of this decrease in Cmaxis unknown.

Excretion

Tetracyclines are concentrated in bile by the liver and excreted in the urine and feces at high concentrations and in a biologically active form.

Excretion of doxycycline by the kidney is about 40% per 72 hours in individuals with a creatinine clearance of about 75 mL per minute. This percentage may fall as low as 1% per 72 hours to 5% per 72 hours in individuals with a creatinine clearance below 10 mL per minute. Studies have shown no significant difference in the serum half-life of doxycycline (range 18 to 22 hours) in individuals with normal and severely impaired renal function. Hemodialysis does not alter the serum half-life.

Pediatric Patients

Population pharmacokinetic analysis of sparse concentration-time data of doxycycline following standard of care intravenous and oral dosing in 44 children (2-18 years of age) showed that allometrically-scaled clearance of doxycycline in children ≥2 to ≤8 years of age (median [range] 3.58 [2.27-10.82] L/h/70 kg, N=11) did not differ significantly from children >8 to 18 years of age (3.27 [1.11-8.12] L/h/70 kg, N=33). For pediatric patients weighing ≤45 kg, body weight normalized doxycycline CL in those ≥2 to ≤8 years of age (median [range] 0.071 [0.041-0.202] L/kg/h, N=10) did not differ significantly from those >8 to 18 years of age (0.081 [0.035-0.126] L/kg/h, N=8). In pediatric patients weighing >45 kg no clinically significant differences in body weight normalized doxycycline CL were observed between those ≥2 to ≤8 years (0.050 L/kg/h, N=1) and those >8 years of age (0.044 [0.014-0.121] L/kg/h, N=25). No clinically significant difference in CL differences between oral and IV were observed in the small cohort of pediatric patients who received the oral (N=19) or IV (N=21) formulation alone.

12.4 Microbiology

Mechanism of Action

Doxycycline inhibits bacterial protein synthesis by binding to the 30S ribosomal subunit. Doxycycline has bacteriostatic activity against a broad range of Gram-positive and Gram-negative bacteria.

Resistance

Cross resistance with other tetracyclines is common.

Antimicrobial Activity

Doxycycline has been shown to be active against most isolates of the following microorganisms, both in vitro and in clinical infections [see Indications and Usage (1)].

Gram-negative bacteria

Acinetobacterspecies

Bartonella bacilliformis

Brucellaspecies

Campylobacter fetus

Enterobacter aerogenes

Escherichia coli

Francisella tularensis

Haemophilus ducreyi

Haemophilus influenzae

Klebsiella granulomatis

Klebsiellaspecies

Neisseria gonorrhoeae

Shigellaspecies

Vibrio cholerae

Yersinia pestis

Gram-positive bacteria

Bacillus anthracis

Listeria monocytogenes

Streptococcus pneumoniae

Anaerobic bacteria

Clostridiumspecies

Fusobacterium fusiforme

Propionibacterium acnes

Other bacteria

Nocardiae andother aerobic Actinomycesspecies

Borrelia recurrentis

Chlamydophila psittaci

Chlamydia trachomatis

Mycoplasma pneumoniae

Rickettsiaespecies

Treponema pallidum

Treponemapallidumsubspecies pertenue

Ureaplasma urealyticum

Parasites

Balantidium coli

Entamoebaspecies

Plasmodium falciparum*
*Doxycycline has been found to be active against the asexual erythrocytic forms of Plasmodium falciparum, but not against the gametocytes of P. falciparum. The precise mechanism of action of the drug is not known.

Susceptibility Testing

For specific information regarding susceptibility test interpretive criteria, and associated test methods and quality control standards recognized by FDA for this drug, please see: http://www.fda.gov/STIC.

13 NONCLINICAL TOXICOLOGY

13.1 Carcinogenesis, Mutagenesis, Impairment of Fertility

Long-term studies in animals to evaluate carcinogenic potential of doxycycline hyclate have not been conducted.

However, a 2 year carcinogenicity study with doxycycline administered daily by oral gavage to adult rats (20, 75, 200 mg/kg/day) demonstrated an increase in uterine polyps in female rats at 200 mg/kg/day (10 times the maximum recommended daily adult dose of doxycycline hyclate based on body surface area comparison) with no change in tumor incidence in male rats at the same dose. A 2-year carcinogenicity study with doxycycline administered daily by oral gavage to adult male (maximum dose 150 mg/kg/day) and female (maximum dose 300 mg/kg/day) mice showed no changes in tumor incidence, at approximately 4 and 7 times the maximum recommended daily adult dose of doxycycline hyclate , based on a body surface area comparison, respectively .

Mutagenesis and fertility studies have not been conducted with doxycycline hyclate. Mutagenesis studies with doxycycline demonstrated no potential to cause genetic toxicity in an in vitropoint mutation study with mammalian cells or in an in vivomicronucleus assay in CD-1 mice. However, data from an in vitromammalian chromosomal aberration assay conducted in CHO cells suggest that doxycycline is a weak clastogen. Oral administration of doxycycline to Sprague-Dawley rats showed adverse effects on fertility and reproduction including increased time for mating, reduced sperm motility, velocity and concentration as well as increased pre and post implantation loss. Reduced sperm velocity was seen at the lowest dosage tested, 50 mg/kg/day which is 2.5 times the maximum recommended daily adult dose of doxycycline hyclate. Although doxycycline impairs the fertility of rats when administered at sufficient dosages, the effect of doxycycline hyclate on human fertility is unknown.

13.2 Animal Toxicology and/or Pharmacology

Hyperpigmentation of the thyroid has been produced by members of the tetracycline-class in the following species: in rats by oxytetracycline, doxycycline, tetracycline PO4, and methacycline; in minipigs by doxycycline, minocycline, tetracycline PO4, and methacycline; in dogs by doxycycline and minocycline; in monkeys by minocycline.

Minocycline, tetracycline PO4, methacycline, doxycycline, tetracycline base, oxytetracycline HCl, and tetracycline HCl, were goitrogenic in rats fed a low iodine diet. This goitrogenic effect was accompanied by high radioactive iodine uptake. Administration of minocycline also produced a large goiter with high radioiodine uptake in rats fed a relatively high iodine diet.

Treatment of various animal species with this class of drugs has also resulted in the induction of thyroid hyperplasia in the following: in rats and dogs (minocycline); in chickens (chlortetracycline); and in rats and mice (oxytetracycline). Adrenal gland hyperplasia has been observed in goats and rats treated with oxytetracycline.

Results of animal studies indicate that tetracyclines cross the placenta and are found in fetal tissues.

15 REFERENCES

1. Friedman JM, Polifka JE. Teratogenic Effects of Drugs. A Resource for Clinicians (TERIS). Baltimore, MD: The Johns Hopkins University Press: 2000: 149-195.
2. Cziezel AE and Rockenbauer M. Teratogenic study of doxycycline. Obstet Gynecol 1997; 89: 524-528.
3. Horne HW Jr. and Kundsin RB. The role of mycoplasma among 81 consecutive pregnancies: a prospective study. Int J Fertil1980; 25: 315-317.
4. Drugs and Lactation Database (LactMed) [Internet]. Bethesda (MD): National Library of Medicine (US); [Last Revision Date 2018 Oct 31; cited 2019 Jun]. Doxycycline; LactMed Record Number: 100; [about 3 screens]. Available from: http://toxnet.nlm.nih.gov/newtoxnet/lactmed.htm

16 HOW SUPPLIED/STORAGE AND HANDLING

How Supplied

Doxycycline Hyclate Tablets, USP 75 mg are round convex light blue, film-coated, compressed tablet with “ 75” debossed on one side of the tablet and "AQ"over "101"debossed on the other. Each 75 mg tablet contains 86.6 mg of doxycycline hyclate equivalent to 75 mg of doxycycline.

Bottles of 20 tablets: NDC 62135-907-20

Doxycycline Hyclate Tablets, USP 150 mg are capsule-shaped, convex, mossy-green, film-coated compressed tablet. Each side of the tablet is trisected with an " A" debossed on each portion of one side of the tablet, and no debossing on the other. Each 150 mg tablet contains 173.1 mg of doxycycline hyclate equivalent to 150 mg of doxycycline.

Bottles of 20 tablets: NDC 62135-908-20

Doxycycline Hyclate Capsules, USP 75 mg are size #2, hard gelatin capsules, blue opaque cap with white opaque body, imprinted with “ CE” on the cap and “ 227” on the body in black ink, filled with yellow powder .Each 75 mg capsule contains 86.6 mg of doxycycline hyclate equivalent to 75 mg of doxycycline.

Bottles of 20 capsules: NDC 62135-975-20

Storage

Store at 20° to 25°C (68° to 77°F) excursions permitted to 15° to 30°C (59° to 86°F) [See USP Controlled Room Temperature]. Protect from light and moisture. Dispense in a tight, light-resistant container as defined in the USP using a child-resistant closure.

17 PATIENT COUNSELING INFORMATION

Advise the patient to read the FDA-approved patient labeling (Instructions for Use).

Important Administration and Safety Information for Patients and Caregivers

Advise patients taking doxycycline hyclate for malaria prophylaxis:

- that no present-day antimalarial agent, including doxycycline, guarantees protection against malaria.
- to avoid being bitten by mosquitoes by using personal protective measures that help avoid contact with mosquitoes, especially from dusk to dawn (for example, staying in well-screened areas, using mosquito nets, covering the body with clothing, and using an effective insect repellent).
- that doxycycline prophylaxis:
  - should begin 1 day to 2 days before travel to the malarious area,
  - should be continued daily while in the malarious area and after leaving the malarious area,
  - should be continued for 4 further weeks to avoid development of malaria after returning from an endemic area,
  - should not exceed 4 months.

Advise all patients taking doxycycline hyclate:

- that doxycycline hyclate tablets (150 mg) can be broken into two-thirds or one-third at the scored lines to provide 100 mg or 50 mg strength doses, respectively.
- that they must swallow doxycycline hyclate capsules whole. They must not break, open, crush, dissolve or chew the capsule [see Dosage and Administration (2.2)] .
- to avoid excessive sunlight or artificial ultraviolet light while receiving doxycycline and to discontinue therapy if phototoxicity (for example, skin eruptions, etc.) occurs. Sunscreen or sunblock should be considered [see Warnings and Precautions (5.4)].
- to drink fluids liberally along with doxycycline hyclate to reduce the risk of esophageal irritation and ulceration [see Adverse Reactions (6)] .
- that the absorption of tetracyclines is reduced when taken with foods, especially those that contain calcium [see Drug Interactions (7.3)]. However, the absorption of doxycycline is not markedly influenced by simultaneous ingestion of food or milk [see Clinical Pharmacology (12.3)] .
- that if gastric irritation occurs, doxycycline hyclate may be given with food or milk [see Clinical Pharmacology (12.3)].
- that the absorption of tetracyclines is reduced when taken with antacids containing aluminum, calcium or magnesium, bismuth subsalicylate, and iron-containing preparations [see Drug Interactions (7.3)].
- that the use of doxycycline might increase the incidence of vaginal candidiasis.

Tooth Discoloration and Inhibition of Bone Growth

Advise patients that doxycycline hyclate, like other tetracycline-class drugs, may cause permanent tooth discoloration of deciduous teeth and reversible inhibition of bone growth when administered during pregnancy. Tell your healthcare provider right away if you become pregnant during treatment [see Warnings and Precautions (5.1, 5.2) and Use in Specific Populations (8.1, 8.4)] .

Lactation

Advise women not to breastfeed during treatment with doxycycline hyclate and for 5 days after the last dose [see Use in Specific Populations (8.2)] .

Diarrhea

Advise patients that diarrhea is a common problem caused by antibacterial drugs which usually ends when the antibacterial is discontinued. Sometimes after starting treatment with antibacterial drugs, patients can develop watery and bloody stools (with or without stomach cramps and fever) even as late as two or more months after having taken the last dose of antibacterial. If this occurs, patients should contact their physician as soon as possible.

Development of Resistance

Counsel patients that antibacterial drugs including doxycycline hyclate should only be used to treat bacterial infections. They do not treat viral infections (for example, the common cold). When doxycycline hyclate are prescribed to treat a bacterial infection, patients should be told that although it is common to feel better early in the course of therapy, the medication should be taken exactly as directed. Skipping doses or not completing the full course of therapy may (1) decrease the effectiveness of the immediate treatment and (2) increase the likelihood that bacteria will develop resistance and will not be treatable by doxycycline hyclate or other antibacterial drugs in the future.

Manufactured for:

Chartwell RX, LLC.

Congers, NY 10920

Rev. 04/2025-01

L72474

Print Instructions for Use at: www.chartwellpharma.com/our-products/

PATIENT INFORMATION

Print Instructions for Use at: www.chartwellpharma.com/our-products/

FDA-Approved Patient Labeling

Instructions for Use

Doxycycline Hyclate Tablets, USP

for oral use

Read this Instructions for Use before you start using doxycycline hyclate and each time you get a refill. There may be new information. This information does not take the place of talking to your healthcare provider about your medical condition or treatment.

Note:

- Your healthcare provider may need to change your dose of doxycycline hyclate during treatment as needed.
- Doxycycline hyclate tablets can be taken whole or broken at scored lines.
- Doxycycline hyclate tablets are marked with scored lines and may be broken at these scored lines to provide the following doses:

150 mg treatment (take the entire whole tablet)

100 mg treatment (take two-thirds of the tablet)

50 mg treatment (take one-third of the tablet)

How to break your doxycycline hyclate tablet:

- Hold the tablet between your thumb and index finger close to the scored line for your dose of doxycycline hyclate as shown above.
- Apply enough pressure to break the tablet at the scored line.
- Do notbreak the doxycycline hyclate tablet in any other way.

Manufactured for:

Chartwell RX, LLC.

Congers, NY 10920

This Instructions for Use has been approved by the U.S. Food and Drug Administration.

Rev. 03/2025

L72475

Rx only

PRINCIPAL DISPLAY PANEL

Doxycycline Hyclate Tablets, USP 75 mg - NDC 62135-907-20 - 20s Tabs Bottle Label

Doxycycline Hyclate Tablets, USP 150 mg - NDC 62135-908-20 - 20s Tabs Bottle Label

Doxycycline Hyclate Capsules, USP 75 mg - NDC 62135-975-20 - 20s caps Bottle Label